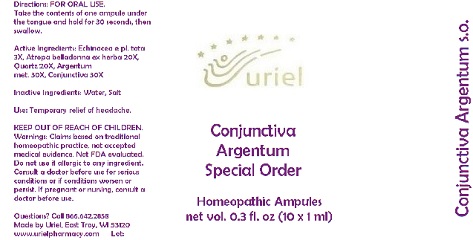 DRUG LABEL: Conjunctiva Argentum Special Order
NDC: 48951-3121 | Form: LIQUID
Manufacturer: Uriel Pharmacy Inc.
Category: homeopathic | Type: HUMAN OTC DRUG LABEL
Date: 20170731

ACTIVE INGREDIENTS: ECHINACEA, UNSPECIFIED 3 [hp_X]/1 mL; ATROPA BELLADONNA 20 [hp_X]/1 mL; SILICON DIOXIDE 20 [hp_X]/1 mL; SILVER 30 [hp_X]/1 mL; BOS TAURUS EYE 30 [hp_X]/1 mL
INACTIVE INGREDIENTS: WATER; SODIUM CHLORIDE

Conjunctiva Argentum Special Order

INDICATIONS AND USAGE

Directions: FOR ORAL USE.

DOSAGE AND ADMINISTRATION

Take the contents of one ampule under the tongue and hold for 30 seconds, then swallow.

ACTIVE INGREDIENT

Active Ingredients: Echinacea e pl. tota 3X, Atropa belladonna ex herba 20X, Quartz 20X, Argentum met. 30X, Conjunctiva 30X

Inactive Ingredients: Water, Salt

PURPOSE

Use: Temporary relief of headache.

KEEP OUT OF REACH OF CHILDREN.

WARNINGS

Warnings: Claims based on traditional homeopathic practice, not accepted medical evidence. Not FDA evaluated. Do not use if allergic to any ingredient. Consult a doctor before use for serious conditions or if conditions worsen or persist. If pregnant or nursing, consult a doctor before use.

QUESTIONS

Questions? Call 866.642.2858 Made by Uriel, East Troy, WI 53120 www.urielpharmacy.com